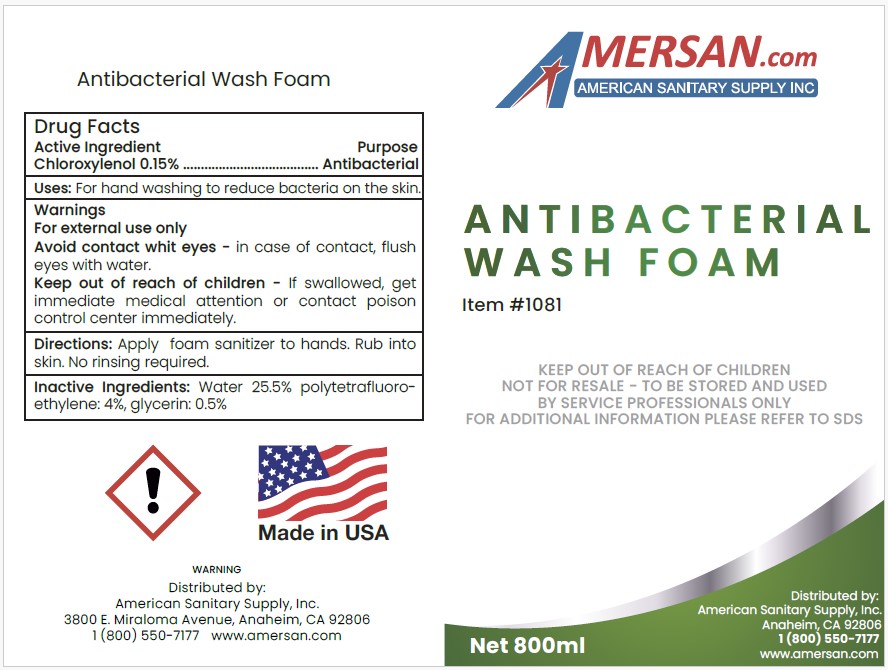 DRUG LABEL: ANTIBACTERIAL WASH FOAM

NDC: 50536-181 | Form: SOLUTION
Manufacturer: AMERICAN CHEMICAL AND SANITARY SUPPLY INC
Category: otc | Type: HUMAN OTC DRUG LABEL
Date: 20250423

ACTIVE INGREDIENTS: CHLOROXYLENOL 0.15 g/100 mL
INACTIVE INGREDIENTS: WATER; POLYTETRAFLUOROETHYLENE; GLYCERIN

ACSS (as PLD) - ANTIBACTERIAL WASH FOAM (50536-181)

ACTIVE INGREDIENT

CHLOROXYLENOL 0.15%

PURPOSE

ANTIBACTERIAL

USES

For hand washing to reduce bacteria on the skin.

WARNINGS

FOR EXTERNAL USE ONLY.

Avoid contact with eyes - in case of contact, flush eyes with water.

Keep out of reach of children - If swallowed, get immediate medical attention or contact poison control center immediately.

DIRECTIONS

Apply foam sanitizer to hands. Rub into skin. No rinsing required.

INACTIVE INGREDIENTS

Water 25.5% polytetrafluoroethylene: 4%, glycerin: 0.5%